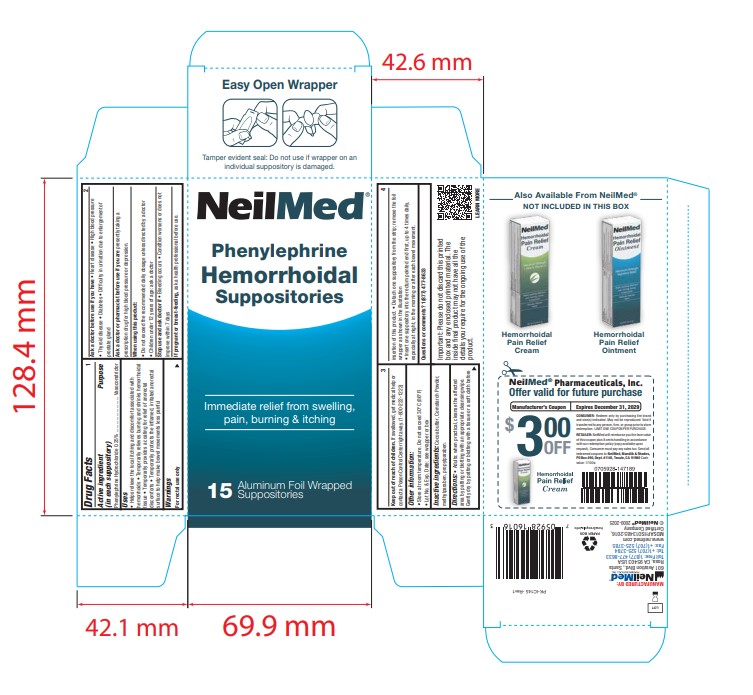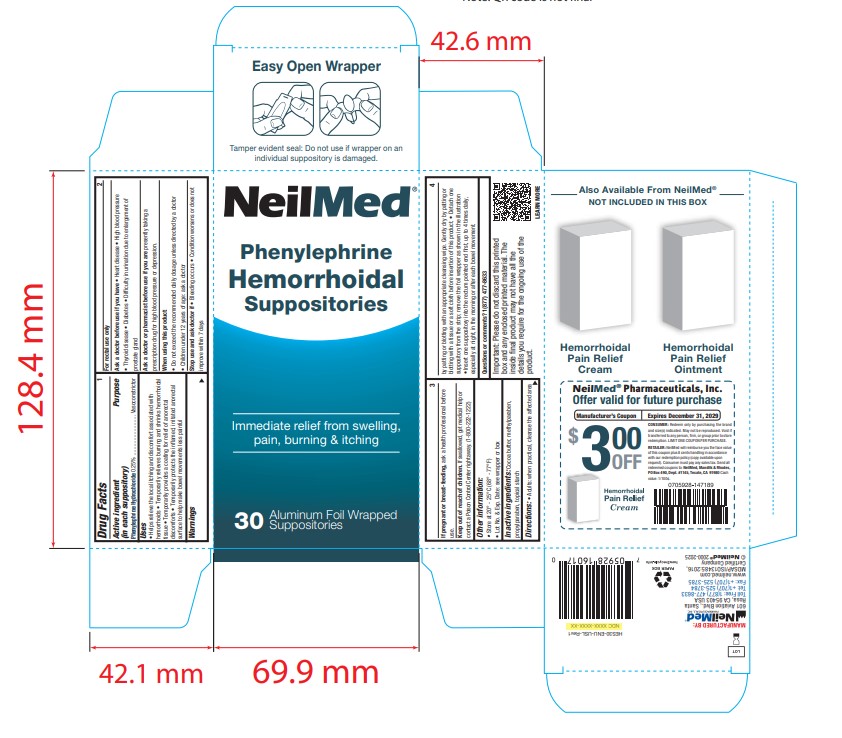 DRUG LABEL: Phenylephrine Hemorrhoidal
NDC: 13709-330 | Form: SUPPOSITORY
Manufacturer: Neilmed Pharmaceuticals Inc.
Category: otc | Type: HUMAN OTC DRUG LABEL
Date: 20250620

ACTIVE INGREDIENTS: PHENYLEPHRINE HYDROCHLORIDE 5 mg/2 g
INACTIVE INGREDIENTS: COCOA BUTTER; PROPYLPARABEN; STARCH, CORN; METHYLPARABEN

Phenylephrine Hemorrhoidal foil wrapped Suppositories

Drug Facts:

Active ingredient Purpose

(in each suppository)

Phenylephrine Hydrochloride 0.25% ........................... Vasoconstrictor

Uses

- Helps relieve the local itching and discomfort associated with hemorrhoids
- Temporarily relieves burning and shrinks hemorrhoidal tissue
- Temporarily provides a coating for relief of anorectal discomforts
- Temporarily protects the inflamed, irritated anorectal surface to help make bowel movements less painful

Warnings

For rectal use only

Ask a doctor before use if you have

• Heart disease • High blood pressure • Thyroid disease • Diabetes • Difficulty in urination due to enlargement of prostate gland

Ask a doctor or pharmacist before use if you are

presently taking a prescription drug for high blood pressure or depression.

When using this product:

• Do not exceed the recommended daily dosage unless directed by a doctor • Children under 12 years of age: ask a doctor

Stop use and ask doctor if

• Bleeding occurs • Condition worsens or does not improve within 7 days

If pregnant or breast-feeding,

ask a health professional before use.

Keep out of reach of children.

. If swallowed, get medical help or contact a Poison Control Center right away. (1-800-222-1222)

Other information:

• Store at 20° - 25°C (68° - 77°F)

• Lot No. & Exp. Date: see wrapper or box

Inactive ingredients:

Cocoa butter, methylparaben, propylparaben, topical starch

Directions:

• Adults: when practical, cleanse the affected area by patting or blotting with an appropriate cleansing wipe. Gently dry by patting or blotting with a tissue or a soft cloth before insertion of this product. • Detach one suppository from the strip; remove the foil wrapper as shown in the illustration • Insert one suppository into the rectum pointed end first, up to 4 times daily, especially at night, in the morning or after each bowel movement.

Important:

Please do not discard this printed box and any enclosed printed material. The inside final product may not have all the details you require for the ongoing use of the product.

Purpose

Purpose - Vasoconstrictor

Package Label